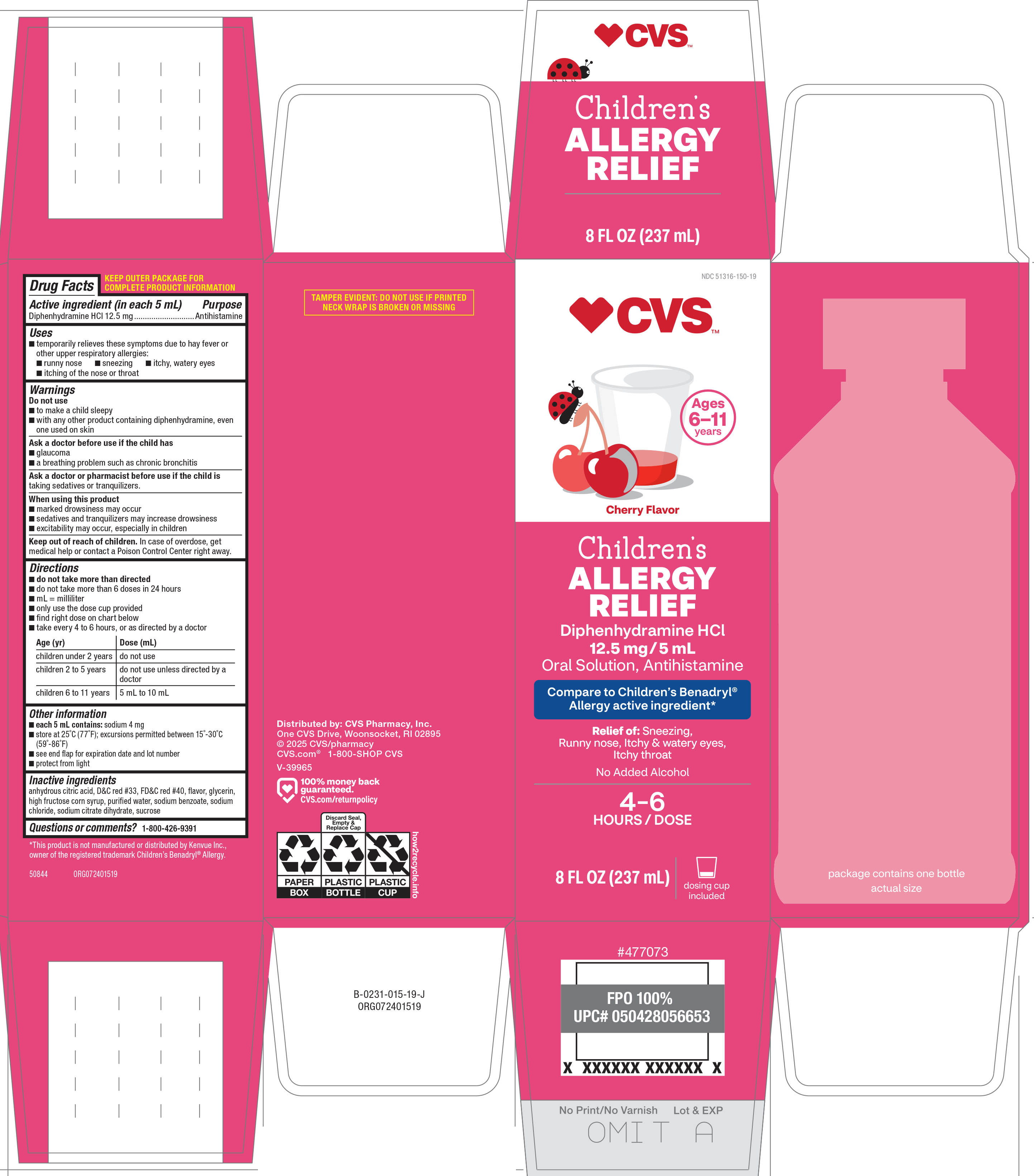 DRUG LABEL: Allergy Relief
NDC: 51316-150 | Form: SOLUTION
Manufacturer: CVS WOONSOCKET PRESCRIPTION CENTER, INCORPORATED
Category: otc | Type: HUMAN OTC DRUG LABEL
Date: 20260217

ACTIVE INGREDIENTS: DIPHENHYDRAMINE HYDROCHLORIDE 12.5 mg/5 mL
INACTIVE INGREDIENTS: ANHYDROUS CITRIC ACID; D&C RED NO. 33; FD&C RED NO. 40; GLYCERIN; HIGH FRUCTOSE CORN SYRUP; WATER; SODIUM BENZOATE; SODIUM CHLORIDE; TRISODIUM CITRATE DIHYDRATE; SUCROSE

CVS 44-015

Active ingredient (in each 5 mL)

Diphenhydramine HCl 12.5 mg

Purpose

Antihistamine

Uses

- temporarily relieves these symptoms due to hay fever or other upper respiratory allergies:
  - runny nose
  - sneezing
  - itchy, watery eyes
  - itching of the nose or throat

Warnings

Do not use

- to make a child sleepy
- with any other product containing diphenhydramine, even one used on skin

Ask a doctor before use if the child has

- glaucoma
- a breathing problem such as chronic bronchitis

Ask a doctor or pharmacist before use if the child is

taking sedatives or tranquilizers.

When using this product

- marked drowsiness may occur
- sedatives and tranquilizers may increase drowsiness
- excitability may occur, especially in children

Keep out of reach of children.

In case of overdose, get medical help or contact a Poison Control Center right away.

Directions

- do not take more than directed
- do not take more than 6 doses in 24 hours
- mL = milliliter
- only use the dose cup provided
- find right dose on chart below
- take every 4 to 6 hours, or as directed by a doctor

Age (yr) | Dose (mL)
children under 2 years | do not use
children 2 to 5 years | do not use unless directed by a doctor
children 6 to 11 years | 5 mL to 10 mL

Other information

- each 5 mL contains: sodium 4 mg
- store at 25°C (77°F); excursions permitted between 15°-30°C (59°-86°F)
- see end flap for expiration date and lot number
- protect from light

Inactive ingredients

anhydrous citric acid, D&C red #33, FD&C red #40, flavor, glycerin, high fructose corn syrup, purified water, sodium benzoate, sodium chloride, sodium citrate dihydrate, sucrose

Questions or comments?

1-800-426-9391

Principal display panel

♥CVS™

Compare to Children’s Benadryl® Allergy active ingredient*

NDC 51316-150-19

Children’s
Allergy
Relief
DIPHENHYDRAMINE HCl
12.5 mg/5 mL
ORAL SOLUTION
Antihistamine

Relief of: Sneezing Runny, nose Itchy, watery eyes
Itchy throat

Ages 6 to 11 Years

Cherry Flavored
Dosage Cup Included
No added alcohol

4–6
HOURS / DOSE

TAMPER EVIDENT: DO NOT USE IF IMPRINTED SAFETY
SEAL UNDER CAP IS BROKEN OR MISSING

Distributed by: CVS Pharmacy, Inc.
One CVS Drive, Woonsocket, RI 02895
© 2025 CVS/pharmacy
CVS.com® 1-800-SHOP CVS
V-39965

♥ 100% money back
guaranteed.
CVS.com/returnpolicy

*This product is not manufactured or distributed by Kenvue Inc.,
owner of the registered trademark Children’s Benadryl® Allergy.

50844 ORG072401519

cvs 44-015